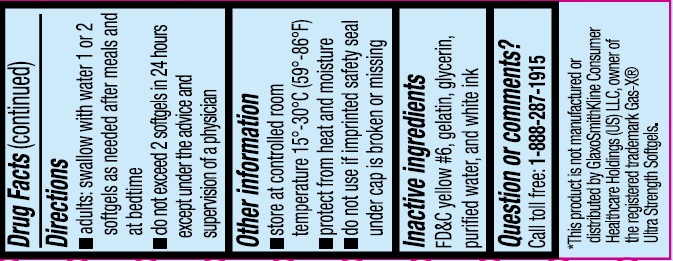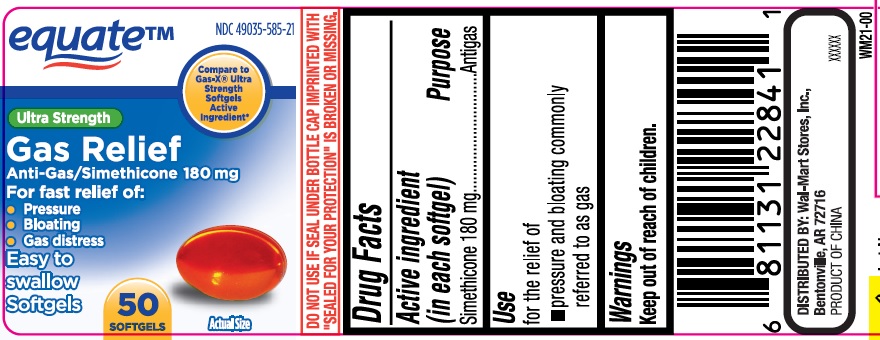 DRUG LABEL: Ultra Strength Gas Relief
NDC: 49035-585 | Form: CAPSULE, LIQUID FILLED
Manufacturer: Wal-Mart Stores Inc
Category: otc | Type: HUMAN OTC DRUG LABEL
Date: 20241121

ACTIVE INGREDIENTS: DIMETHICONE 180 mg/1 1
INACTIVE INGREDIENTS: FD&C YELLOW NO. 6; GELATIN; GLYCERIN; WATER

Ultra Strength Gas Relief

Active ingredient (in each softgel)

Simethicone 180 mg

Purpose

Antigas

Use

for the relief of

- pressure and bloating commonly referred to as gas

Warnings

Keep out of reach of children

Directions

- adults: swallow with water 1 or 2 softgels as needed after meals and at bedtime
- do not exceed 2 softgels in 24 hours under the advice and supervision of a physician

Other information

- store at controlled room temperature 15º - 30ºC (59º - 86ºF)
- protect from heat and moisture
- do not use if imprinted safety seal under cap is broken or missing

Inactive ingredients

FD&C yellow#6, gelatin, glycerin, purified water and white ink

Questions or comments?

Call toll free: 1-888-287-1915

PRINCIPAL DISPLAY PANEL

Ultra Strength Gas Relief

Simethicone 180 mg Anti-gas 50 Softgels

NDC 49035-585-21

*Compare to the active ingredient in Gas-X®Ultra Strength